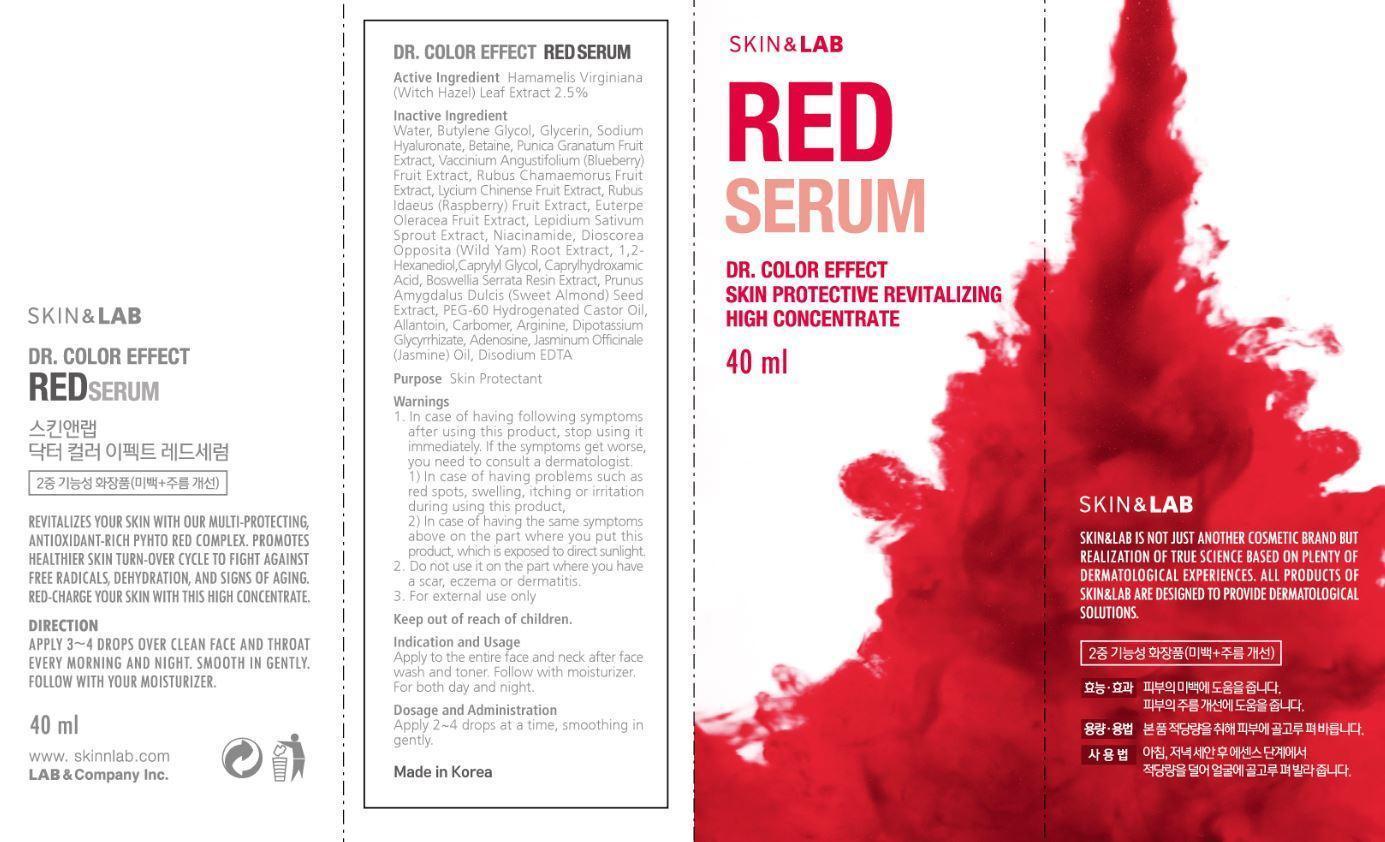 DRUG LABEL: Red Serum
NDC: 69457-000 | Form: GEL
Manufacturer: LAB & Company Inc.
Category: otc | Type: HUMAN OTC DRUG LABEL
Date: 20150318

ACTIVE INGREDIENTS: WITCH HAZEL 2.5 g/100 g
INACTIVE INGREDIENTS: WATER; BUTYLENE GLYCOL; GLYCERIN; HYALURONATE SODIUM; BETAINE; PUNICA GRANATUM WHOLE; VACCINIUM ANGUSTIFOLIUM WHOLE; RUBUS CHAMAEMORUS FRUIT; LYCIUM CHINENSE FRUIT; RUBUS IDAEUS FRUIT VOLATILE OIL; EUTERPE OLERACEA WHOLE; LEPIDIUM SATIVUM LEAF; NIACINAMIDE; DIOSCOREA OPPOSITIFOLIA WHOLE; 1,2-HEXANEDIOL; CAPRYLYL GLYCOL; CAPRYLHYDROXAMIC ACID; BOSWELLIA SERRATA RESIN OIL; ALMOND OIL; PEG-60 HYDROGENATED CASTOR OIL; ALLANTOIN; CARBOMER COPOLYMER TYPE A; ARGININE; GLYCYRRHIZINATE DIPOTASSIUM; ADENOSINE; JASMINUM OFFICINALE WHOLE; EDETATE DISODIUM

Active Ingredient Hamamelis Virginiana (Witch Hazel) Leaf Extract 2.5%

Purpose Skin Protectant

Keep out of reach of children.

Indication and Usage

Apply to the entire face and neck after face wash and toner. Follow with moisturizer. For both day and night.

Dosage and Administration

Apply 2~4 drops at a time, smoothing in gently.

Warnings

1. In case of having following symptoms after using this product, stop using it immediately. If the symptoms get worse, you need to consult a dermatologist.

1) In case of having problems such as red spots, swelling, itching or irritation during using this product.

2) In case of having the same symptoms above on the part where you put this product, which is exposed to direct sunlight.

2. Do not use it on the part where you have a scar, eczema or dermatitis.

3. For external use only.

Inactive Ingredient

water, butylene glycol, glycerin, sodium hyaluronate, betaine, punica granatum fruit extract, vaccinium angustifolium (blueberry) fruit extract, rubus chamaemorus fruit extract, lycium chinense fruit extract, rubus idaeus (raspberry) fruit extract, euterpe oleracea fruit extract, lepidium sativum sprout extract, niacinamide, dioscorea opposita (wild yam) root extract, 1,2-hexanediol, caprylyl glycol, capylhydroxamic acid, boswellia, serrata resin extract, prunus amygdalus dulcis (sweet almond) seed extract, PEG-60 hydrogenated castor oil, allantoin, carbomer, arginine, dipotassium glycyrrhizate, adenosine, jasminum officinale (jasmine) oil, disodium EDTA